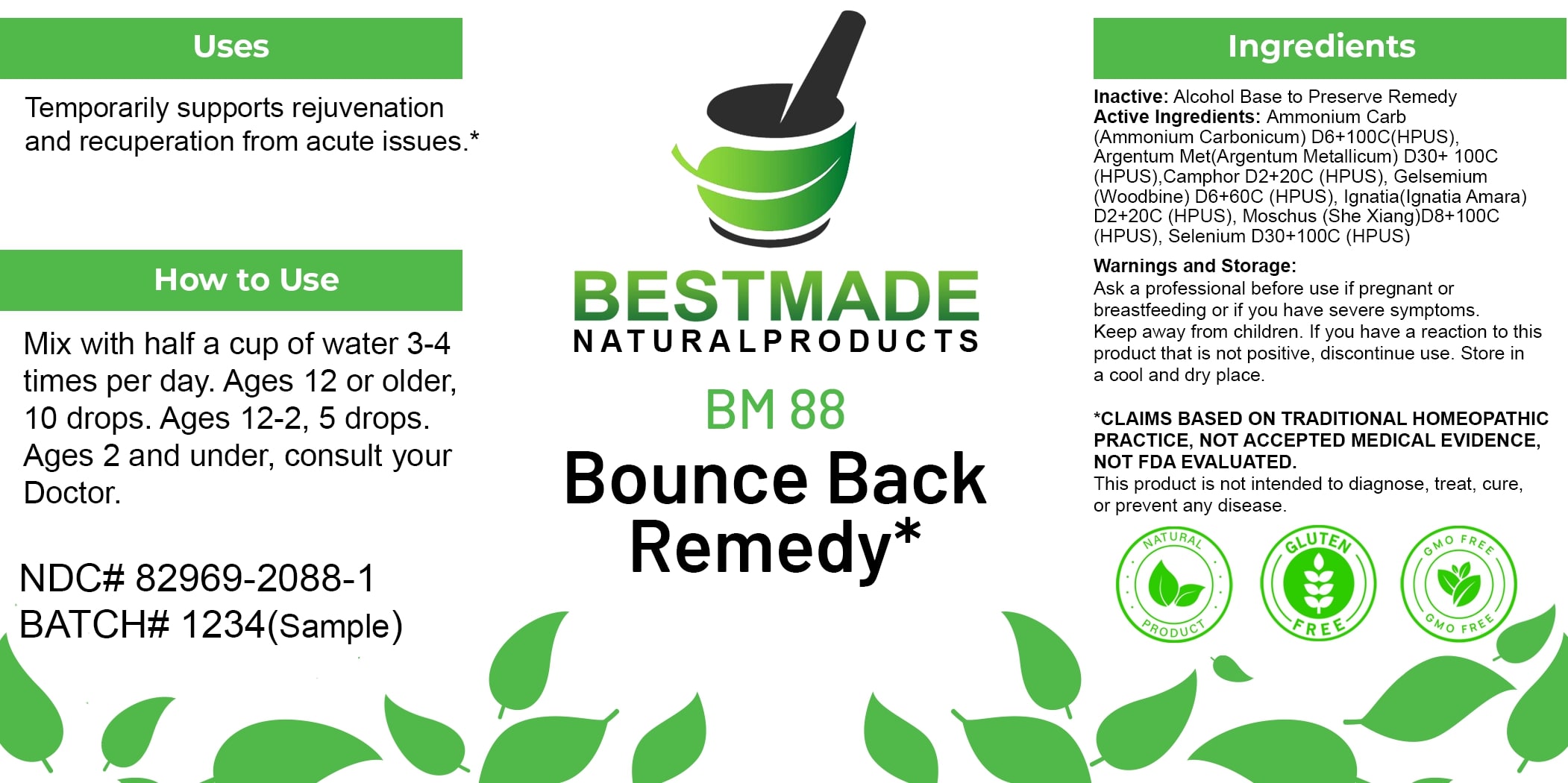 DRUG LABEL: Bestmade Natural Products BM88
NDC: 82969-2088 | Form: LIQUID
Manufacturer: Bestmade Natural Products
Category: homeopathic | Type: HUMAN OTC DRUG LABEL
Date: 20250203

ACTIVE INGREDIENTS: MOSCHUS MOSCHIFERUS MUSK SAC RESIN 30 [hp_C]/30 [hp_C]; CAMPHOR (NATURAL) 30 [hp_C]/30 [hp_C]; STRYCHNOS IGNATII SEED 30 [hp_C]/30 [hp_C]; AMMONIUM CARBONATE 30 [hp_C]/30 [hp_C]; SILVER 30 [hp_C]/30 [hp_C]; SELENIUM 30 [hp_C]/30 [hp_C]; GELSEMIUM SEMPERVIRENS ROOT 30 [hp_C]/30 [hp_C]
INACTIVE INGREDIENTS: ALCOHOL 30 [hp_C]/30 [hp_C]

BM88

DOSAGE AND ADMINISTRATION

How to Use

Mix with half a cup of water 3-4 times per day. Ages 12 or older, 10 drops. Ages 12-2, 5 drops. Ages 2 and under, consult your Doctor.

INACTIVE INGREDIENT

Ingredients

Inactive: Alcohol Base to Preserve Remedy

ACTIVE INGREDIENT

Active Ingredients: Ammonium Carb (Ammonium Carbonicum) D6+100C (HPUS), Argentum Met(Argentum Metallicum) D30+100C (HPUS), Camphor D2+20C (HPUS), Gelsemium (Woodbine) D6+60C (HPUS), Ignatia(Ignatia Amara) D2+20C (HPUS), Moschus (She Xiang)D8+100C (HPUS), Selenium D30+100C (HPUS)

Uses

Temporarily supports rejuvenation and recuperation from acute issues.*

*CLAIMS BASED ON TRADITIONAL HOMEOPATHIC PRACTICE, NOT ACCEPTED MEDICAL EVIDENCE, NOT FDA EVALUATED.

This product is not intended to diagnose, treat, cure, or prevent any disease.

Uses

Temporarily supports rejuvenation and recuperation from acute issues.*

*CLAIMS BASED ON TRADITIONAL HOMEOPATHIC PRACTICE, NOT ACCEPTED MEDICAL EVIDENCE, NOT FDA EVALUATED.

This product is not intended to diagnose, treat, cure, or prevent any disease.

KEEP OUT OF REACH OF CHILDREN

Warnings and Storage:

Ask a professional before use if pregnant or breastfeeding or if you have severe symptoms. Keep away from children. If you have a reaction to this product that is not positive, discontinue use. Store in a cool and dry place.

Warnings and Storage:

Ask a professional before use if pregnant or breastfeeding or if you have severe symptoms. Keep away from children. If you have a reaction to this product that is not positive, discontinue use. Store in a cool and dry place.

*CLAIMS BASED ON TRADITIONAL HOMEOPATHIC PRACTICE, NOT ACCEPTED MEDICAL EVIDENCE, NOT FDA EVALUATED.

This product is not intended to diagnose, treat, cure, or prevent any disease.

Entire package label